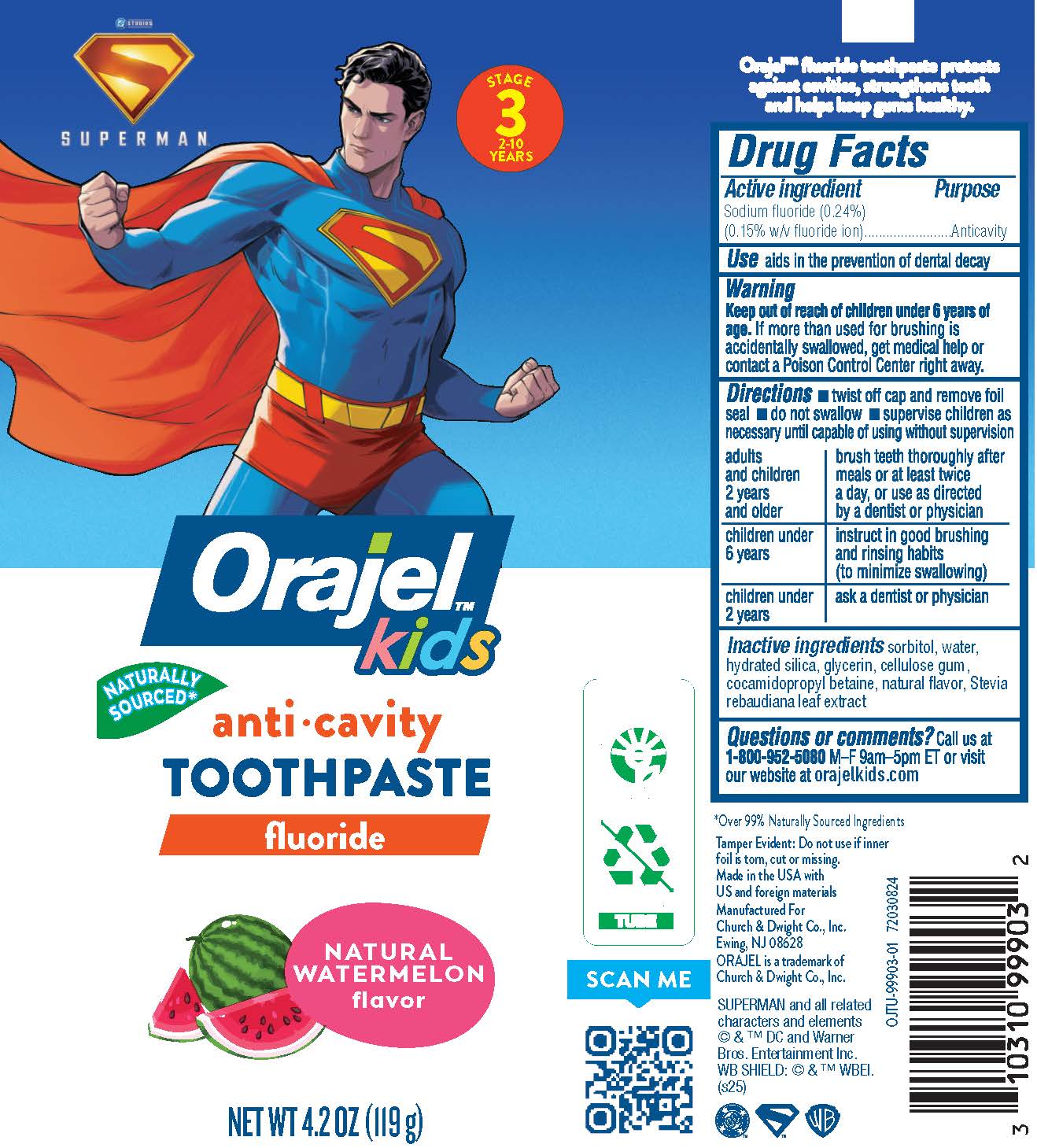 DRUG LABEL: Orajel Kids Superman
NDC: 10237-732 | Form: GEL, DENTIFRICE
Manufacturer: Church & Dwight Co., Inc.
Category: otc | Type: HUMAN OTC DRUG LABEL
Date: 20250109

ACTIVE INGREDIENTS: SODIUM FLUORIDE 1.5 mg/1 g
INACTIVE INGREDIENTS: CELLULOSE GUM; HYDRATED SILICA; STEVIA REBAUDIANA LEAF; SORBITOL; WATER; GLYCERIN; COCAMIDOPROPYL BETAINE

Orajel Kids Superman Toothpaste

ACTIVE INGREDIENT

Sodium fluoride (0.24%)
(0.15% w/v fluoride ion)

PURPOSE

Anticavity

INDICATIONS AND USAGE

aids in the prevention of dental decay

WARNING

Keep out of reach of children under 6 years of age. If more than used for brushing is accidentally swallowed, get medical help or contact a Poison Control Center right away.

DOSAGE AND ADMINISTRATION

■ twist off cap and remove foil seal ■ do not swallow ■ supervise children as necessary until capable of using without supervision

adults and children 2 years and older: brush teeth thoroughly after meals or at least twice a day, or use as directed by a dentist or physician

children under 6 years: instruct in good brushing and rinsing habits (to minimize swallowing)

children under 2 yeras: ask a dentist or physician

INACTIVE INGREDIENT

sorbitol, water, hydrated silica, glycerin, cellulose gum, cocamidopropyl betaine, natural flavor, Stevia rebaudiana leaf extract

PACKAGE LABEL

DC STUDIOS

SUPERMAN

STAGE 3 2-10 YEARS

OrajelTM Kids

anti-cavity

TOOTHPASTE

fluoride

NATURAL WATERMELON flavor

NET WT 4.2 OZ (119 g)